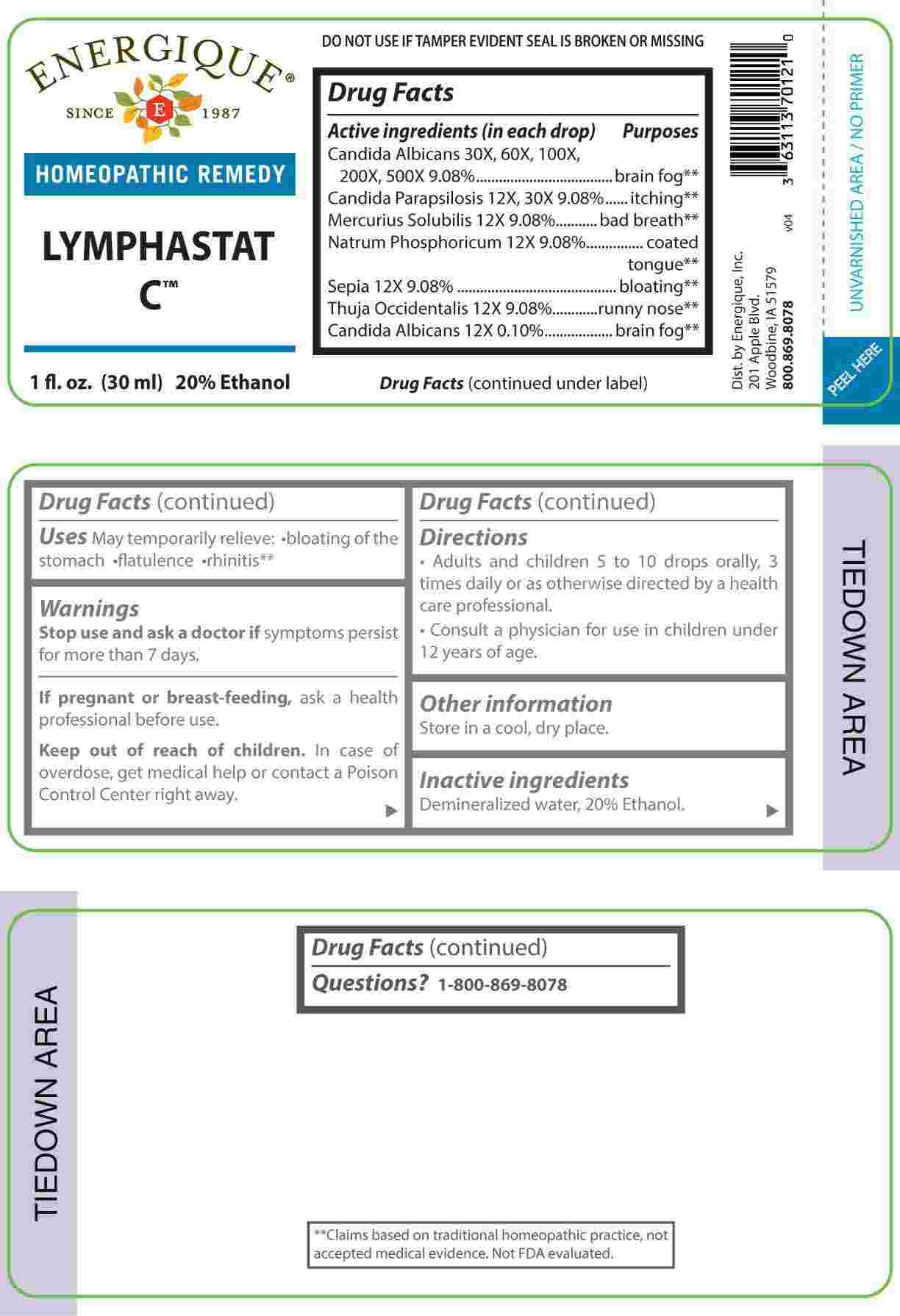 DRUG LABEL: Lymphastat
NDC: 44911-0713 | Form: LIQUID
Manufacturer: Energique, Inc.
Category: homeopathic | Type: HUMAN OTC DRUG LABEL
Date: 20240522

ACTIVE INGREDIENTS: MERCURIUS SOLUBILIS 12 [hp_X]/1 mL; SODIUM PHOSPHATE, DIBASIC, HEPTAHYDRATE 12 [hp_X]/1 mL; SEPIA OFFICINALIS JUICE 12 [hp_X]/1 mL; THUJA OCCIDENTALIS LEAFY TWIG 12 [hp_X]/1 mL; CANDIDA PARAPSILOSIS 12 [hp_X]/1 mL; CANDIDA ALBICANS 12 [hp_X]/1 mL
INACTIVE INGREDIENTS: WATER; ALCOHOL

DRUG FACTS:

ACTIVE INGREDIENTS:

(in each drop) Candida Albicans 30X, 60X, 100X, 200X, 500X 9.08%, Candida Parapsilosis 12X, 30X 9.08%, Mercurius Solubilis 12X 9.08%, Natrum Phosphoricum 12X 9.08%, Sepia 12X 9.08%, Thuja Occidentalis 12X 9.08%, Candida Albicans 12X 0.10%.

PURPOSE:

Candida Albicans – brain fog,** Candida Parapsilosis - itching,** Mercurius Solubilis – bad breath,** Natrum Phosphoricum – coated tongue,** Sepia - bloating,** Thuja Occidentalis – runny nose,**

**Claims based on traditional homeopathic practice, not accepted medical evidence. Not FDA evaluated.

USES:

May temporarily relieve:

• bloating of the stomach • flatulence • rhinitis**

**Claims based on traditional homeopathic practice, not accepted medical evidence. Not FDA evaluated.

WARNINGS:

Stop use and ask a doctor if symptoms persist for more than 7 days.

If pregnant or breast-feeding, ask a health professional before use.

Keep out of reach of children. In case of overdose, get medical help or contact a Poison Control Center right away.

DO NOT USE IF TAMPER EVIDENT SEAL IS BROKEN OR MISSING

Store in a cool, dry place.

KEEP OUT OF REACH OF CHILDREN:

In case of overdose, get medical help or contact a Poison Control Center right away.

DIRECTIONS:

• Adults and children 5 to 10 drops orally, 3 times daily or as otherwise directed by a health care professional.

• Consult a physician for use in children under 12 years of age.

INACTIVE INGREDIENTS:

Demineralized water, 20% Ethanol

QUESTIONS:

Dist. by Energique, Inc.

201 Apple Blvd.

Woodbine, IA 51579

800-869-8078

PACKAGE LABEL DISPLAY:

ENERGIQUE

SINCE 1987

HOMEOPATHIC REMEDY

LYMPHASTAT C

1 fl. oz. (30 ml)